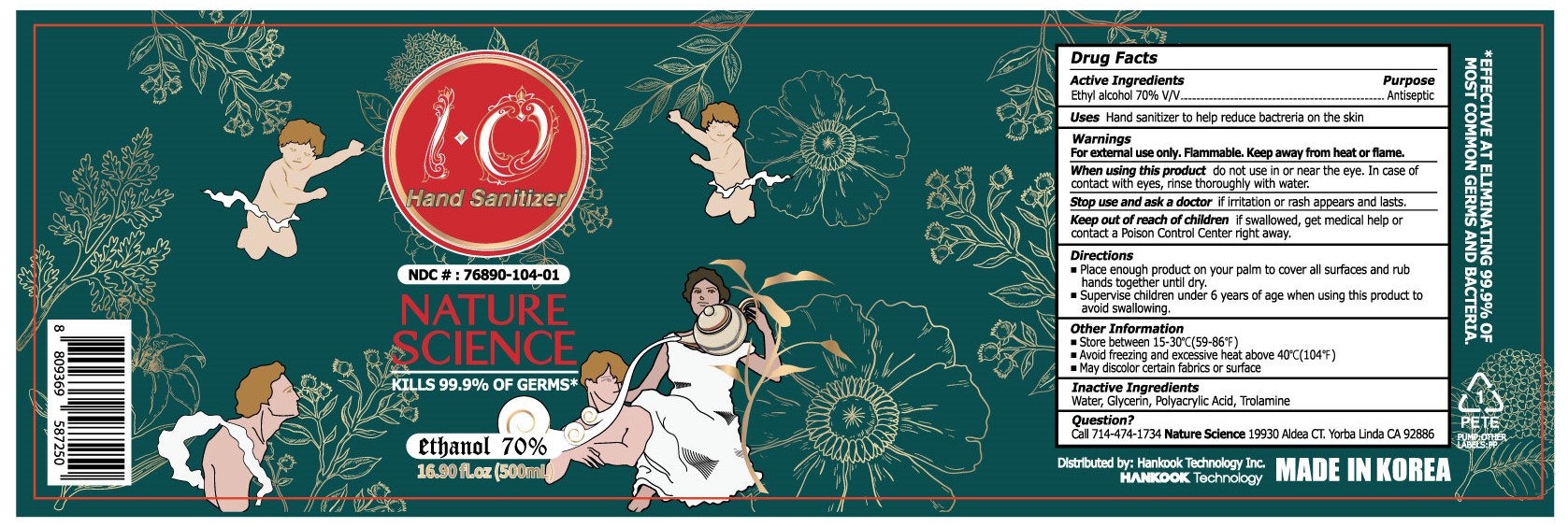 DRUG LABEL: Nature Science IO K1
NDC: 76890-104 | Form: GEL
Manufacturer: HANKOOK Technology Inc.
Category: otc | Type: HUMAN OTC DRUG LABEL
Date: 20200625

ACTIVE INGREDIENTS: ALCOHOL 70 mL/100 mL
INACTIVE INGREDIENTS: GLYCERIN; POLYACRYLIC ACID (250000 MW); WATER; TROLAMINE

Active Ingredient(s)

Ethyl alcohol 70% v/v. Purpose: Antiseptic

Purpose

Antiseptic

Uses

Hand Sanitizer to help reduce bacteria on the skin.

Warnings

For external use only. Flammable. Keep away from heat or flame.

When using this product do not use in or near the eye. In case of contact with eyes, rinse thorougly with water.

Stop use and ask a doctor if irritation or rash appears and lasts.

Keep out of reach of children. If swallowed, get medical help or contact a Poison Control Center right away.

Directions

- Place enough product on palm to cover all surfaces and rub hands together until dry.
- Supervise children under 6 years of age when using this product to avoid swallowing.

Other information

- Store between 15-30C (59-86F)
- Avoid freezing and excessive heat above 40C (104F)
- May discolor certain fabrics or surfaces

Inactive ingredients

Water, Glycerin, Polyacrylic Acid, Trolamine